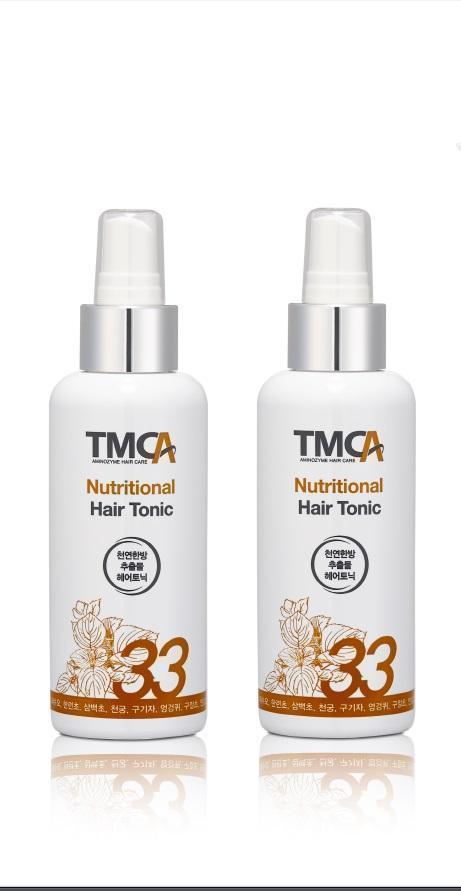 DRUG LABEL: TMC-A Hair Tonic
NDC: 69100-1001 | Form: LIQUID
Manufacturer: Gahwa Well Food Co.,Ltd
Category: otc | Type: HUMAN OTC DRUG LABEL
Date: 20140711

ACTIVE INGREDIENTS: OATMEAL 0.0001 g/100 mL
INACTIVE INGREDIENTS: ONION; RADISH; LYSINE

Drug Facts

ACTIVE INGREDIENT

oatmeal

INACTIVE INGREDIENT

onion bulb ext, radish root ext, oenanthe javanica ext, porato pulp ext, carrot root ext, pear fruit ext, lemon fruit ext, nelumbo nucifera root ext, zanthoxylum schinifolium leaf ext, radish leaf ext, clove flower ext, artemisia vulgaris ext, pinus densiflora leaf ext, polygonum multiflorum root ext, chrysanthellum indicum ext, cnidium officinale root ext, eclipta prostrata ext, ginger root ext, camellia sinensis leaf ext, lycium chinense fruit ext, dodonopsis lancelolata root ext, laminaria japonica ext, saururus chinensis ext, thistle flower/leaf/stem ext, chrysanthemum sibiricum ext, panax ginseng leaf/stem ext, ginkgo biloba leaf ext, acorus calamus root ext, mentha arvensis ext, undaria pinnatifida ext, lysine, proline

PURPOSE

nourishing and moisturizing hair

keep out of reach of the children

INDICATIONS AND USAGE

more than 3 times per a day, spread at the part of hair loss and softly massage
shake well before use

do not use on damaged or broken skin
when using this product keep out of eyes rinse with water to remove
stop use and ask a doctor if rash occurs
do not swallow

DOSAGE AND ADMINISTRATION

for external use only